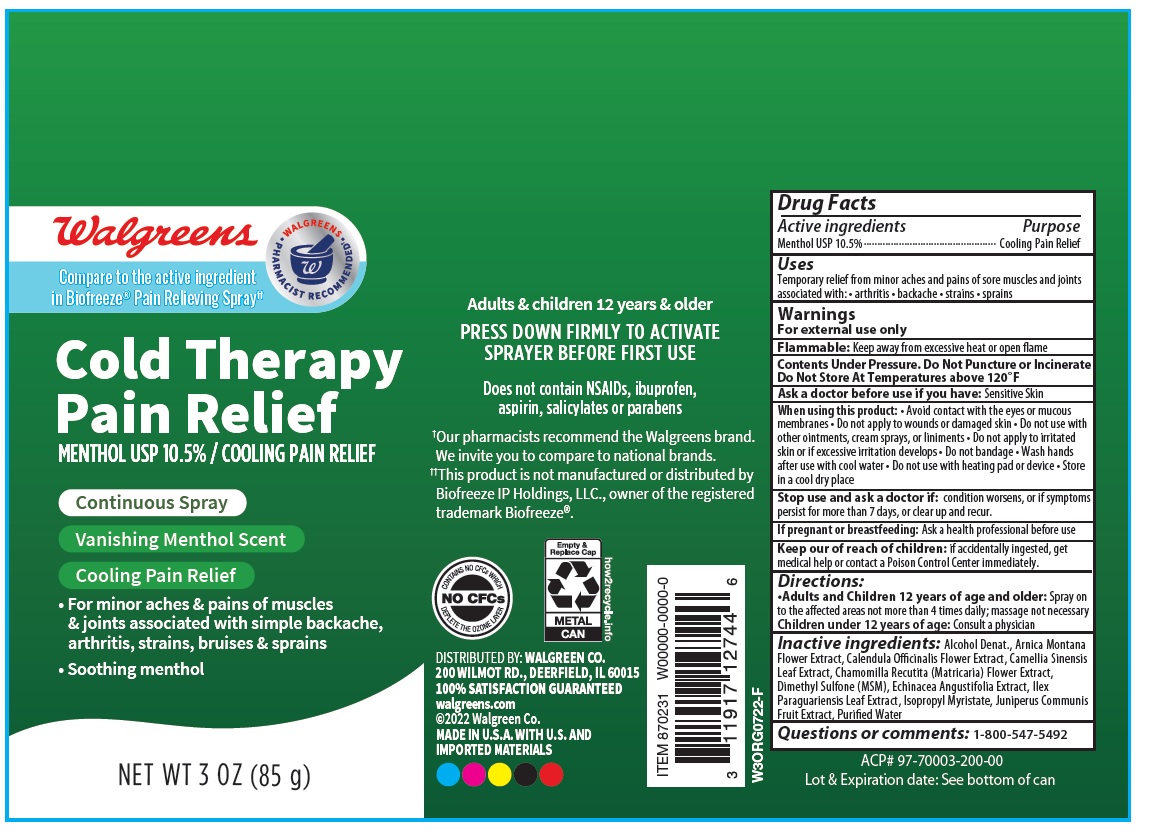 DRUG LABEL: Cold Therapy Pain Relief
NDC: 0363-4411 | Form: SPRAY
Manufacturer: WALGREEN COMPANY
Category: otc | Type: HUMAN OTC DRUG LABEL
Date: 20241231

ACTIVE INGREDIENTS: MENTHOL 10.5 g/100 g
INACTIVE INGREDIENTS: ALCOHOL; ARNICA MONTANA FLOWER; CALENDULA OFFICINALIS FLOWER; GREEN TEA LEAF; MATRICARIA RECUTITA FLOWERING TOP; DIMETHYL SULFONE; ECHINACEA ANGUSTIFOLIA; ILEX PARAGUARIENSIS LEAF; ISOPROPYL MYRISTATE; JUNIPER BERRY; WATER

Drug Facts

Active ingredient Purpose
Menthol 10.5%..............................................................Cooling Pain Relief

PURPOSE

Cooling Pain relief

INDICATIONS AND USAGE

Uses Temporary relief from minor aches and pains of sore muscles and
joints associated with arthritis, backache, strains and sprains

Warnings
For external use only.
Flammable: Do not use while smoking or near heat or flame.
When using this product • avoid contact with the eyes or mucous
membranes • do not apply to wounds or damaged skin • do not apply
to the irritated skin • do not bandage • wash hands after use with cool
water • do not use with heating pad or device
Stop use and ask a doctor if • condition worsens, or if symptoms
persist for more than 7 days, or clear up and reoccur.

Keep out of reach of children. If accidentally ingested get medical help or contact a Poison Control Center immediately

DOSAGE AND ADMINISTRATION

Directions • Adults and children 12 years of age and older: Spray to affected area not more than 4 times daily.

• Children under 12 years of age: Consult physician.

Inactive ingredients Alcohol Denat., Arnica Montana Flower
Extract, Calendula Officinalis Flower Extract, Camellia Sinensis Leaf
Extract, Chamomile Recutita Flower Extract, Dimethyl Sulfone, Echinacea
Angustifolia Extract, Ilex Paraguariensis Leaf Extract, Isopropyl Myristate,
Juniperus Communis Fruit Extract, Water